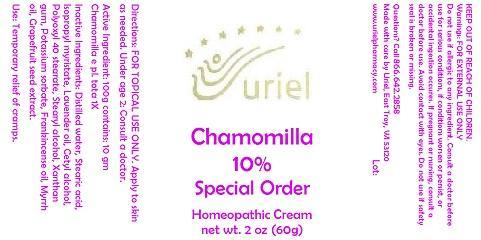 DRUG LABEL: Chamomilla 10 Special Order
NDC: 48951-3059 | Form: CREAM
Manufacturer: Uriel Pharmacy Inc.
Category: homeopathic | Type: HUMAN OTC DRUG LABEL
Date: 20141124

ACTIVE INGREDIENTS: MATRICARIA RECUTITA 1 [hp_X]/1 g
INACTIVE INGREDIENTS: WATER; STEARIC ACID; ISOPROPYL MYRISTATE; LAVENDER OIL; CETYL ALCOHOL; POLYOXYL 40 STEARATE; STEARYL ALCOHOL; XANTHAN GUM; POTASSIUM SORBATE; FRANKINCENSE OIL; MYRRH OIL; CITRUS PARADISI SEED

Chamomilla 10 Special Order

INDICATIONS AND USAGE

Directions: FOR TOPICAL USE ONLY.

DOSAGE AND ADMINISTRATION

Apply to skin as needed. Under age 2: Consult a doctor.

Active Ingredient: 100g contains: 10 gm Chamomilla e pl. tota 1X

INACTIVE INGREDIENT

Inactive Ingredients: Distilled water, Stearic acid, Isopropyl myristate, Lavender oil, Cetyl alcohol, Polyoxyl 40 stearate, Stearyl alcohol, Xanthan gum, Potassium sorbate, Frankincense oil, Myrrh oil, Grapefruit seed extract.

PURPOSE

Use: Temporary relief of cramps.

KEEP OUT OF REACH OF CHILDREN.

WARNINGS

Warnings: FOR EXTERNAL USE ONLY Do not use if allergic to any ingredient. Consult a doctor before use for serious conditions, if conditions worsen or persist, or accidental ingestion occures. If pregnant or nursing, consult a doctor before use. Avoid contact with eyes. Do not use if safety seal is broken or missing.

QUESTIONS

Questions? Call 866.642.2858 Made with care by Uriel, East Troy, WI 53120 www.urielpharmacy.com